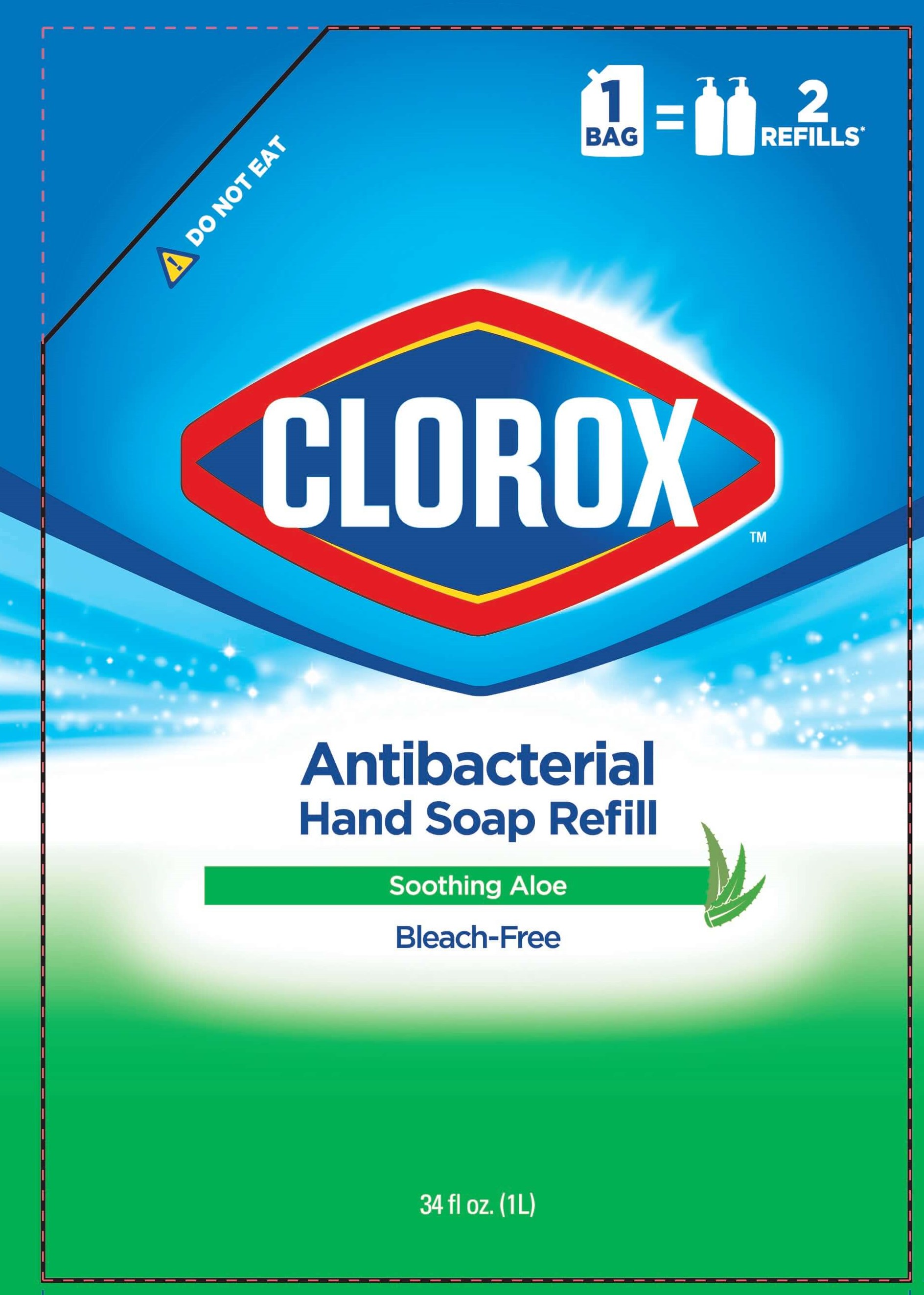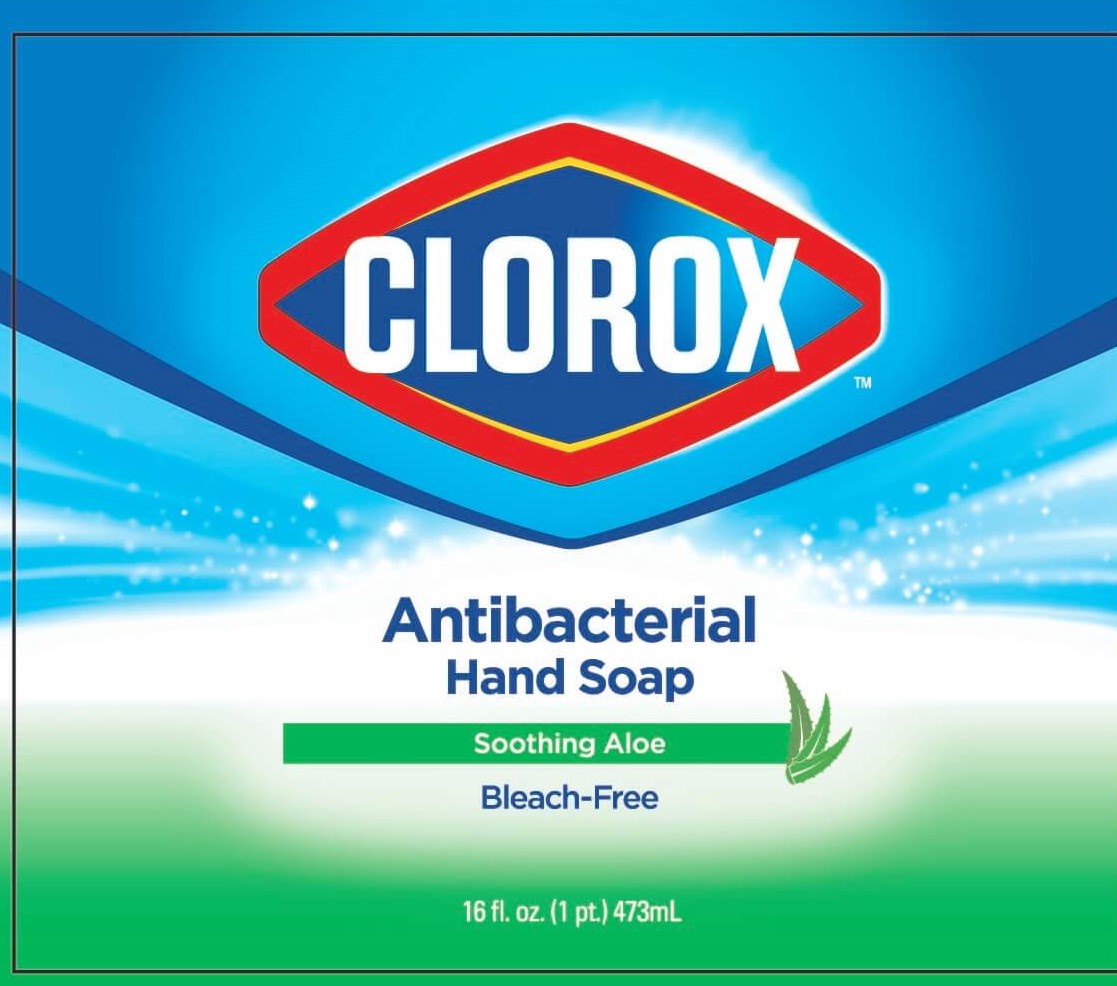 DRUG LABEL: Clorox Antibacterial
NDC: 69540-0033 | Form: SOAP
Manufacturer: Brand Buzz
Category: otc | Type: HUMAN OTC DRUG LABEL
Date: 20221231

ACTIVE INGREDIENTS: CHLOROXYLENOL 0.003 g/1 mL
INACTIVE INGREDIENTS: WATER; SODIUM LAURETH SULFATE; COCAMIDOPROPYL BETAINE; GLYCERIN; COCOYL METHYL MONOETHANOLAMINE; SODIUM CHLORIDE; CITRIC ACID MONOHYDRATE; EDETATE DISODIUM ANHYDROUS; METHYLCHLOROISOTHIAZOLINONE; METHYLISOTHIAZOLINONE; FRAGRANCE FLORAL ORC0902236

Clorox™ Antibacterial Hand Soap (Aloe)

DRUG FACTS

Active Ingredient

Chloroxylenol 0.3%

Purpose

Antibacterial

Use

- for handwashing to decrease bacteria on the skin

Warnings

For external use only.

When using this product avoid contact with the eyes. If contact occurs, rinse eyes with water.

Stop use and ask a doctor if irritation or redness develops and condition persists for more than 72 hours.

Keep out of reach of children. If swallowed, get medical help or contact a Poison Control Center right away.

Directions

- Apply onto wet hands, lather for at least 30 seconds and rinse thoroughly.

Inactive ingredients

WATER, SODIUM LAURETH SULFATE, COCAMIDOPROPYL BETAINE, GLYCERIN, COCAMIDE METHYL MEA, SODIUM CHLORIDE, PARFUM, CHLOROXYLENOL, CITRIC ACID, DISODIUM EDTA, METHYLCHLOROISOTHIAZOLINONE AND METHYLISOTHIAZOLINONE, DYE.

Questions or Comments?

Call us at 1-888-508-4750 or visit us at www.brandbuzzcp.com

Clorox Antibacterial Hand Soap washes away dirt and bacteria from hands. This gentle antibacterial hand soap is perfect for frequent handwahing and leaves a fresh smelling scent.

Developed in USA

Responsibly Made in China ©2021

Distributed by Brand Buzz LLC,
1407 Broadway, New York, NY 10018

The Clorox name and logo are registered trademarks of The Clorox Company and are used under license by Brand Buzz LLC.

PACKAGE LABEL

CLOROX™

Antibacterial

Hand Soap

Soothing Aloe

Bleach-Free

16 fl. oz. (1pt) 473ml

34 fl oz. (1L)